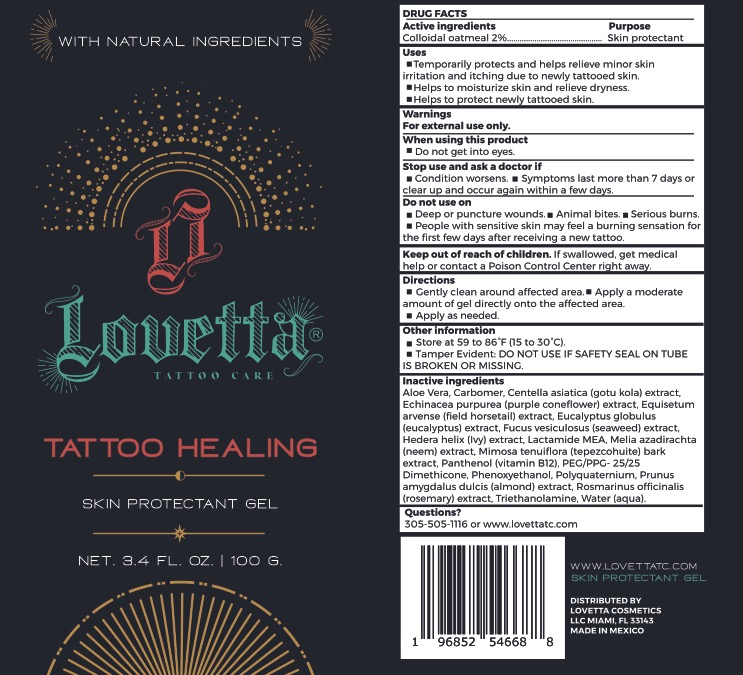 DRUG LABEL: Lovetta Tattoo Healing Skin Protectant
NDC: 82596-200 | Form: GEL
Manufacturer: LOVETTA COSMETICS LLC
Category: otc | Type: HUMAN OTC DRUG LABEL
Date: 20221116

ACTIVE INGREDIENTS: OATMEAL 20 mg/1 g
INACTIVE INGREDIENTS: ROSMARINUS OFFICINALIS FLOWERING TOP; TROLAMINE; WATER; POLIDRONIUM CHLORIDE; ALMOND; ALOE VERA WHOLE; CARBOMER HOMOPOLYMER, UNSPECIFIED TYPE; CENTELLA ASIATICA; ECHINACEA PURPUREA; EQUISETUM ARVENSE TOP; EUCALYPTUS GLOBULUS LEAF; FUCUS VESICULOSUS; HEDERA HELIX FLOWERING TWIG; N-LACTOYL ETHANOLAMINE; AZADIRACHTA INDICA WHOLE; MIMOSA TENUIFLORA BARK; PANTHENOL; PEG/PPG-25/25 DIMETHICONE; PHENOXYETHANOL

Lovetta Tattoo Healing Gel

Active ingredient

Colloidal oatmeal 2%

Purpose

Skin protectant

Uses

■ Temporarily protects and helps relieve minor skin irritation and itching due to newly tattooed skin .

■ Helps to moisturize skin and relieve dryness .

■ Helps to protect newly tattooed skin .

Warnings

For external use only

When using this product

- do not get into eyes

Stop use and ask a doctor if

- condition worsens
- symptoms last more than 7 days or clear up and occur again withing a few days

Keep out of reach of children.

If swallowed, get medical help or contact a Poison Control Center right away.

Directions

■ Gently clean around affected area. ■ Apply a moderate amount of gel directly onto the affected area.

■ Apply as needed.

Inactive ingredients

Aloe Vera, Carbomer , Centella asiatica (gotu kola) extract , Echinacea purpurea (purple coneflower) extract , Equisetum arvense (field horsetail) extract, Eucalyptus globulus (eucalyptus) extract , Fucus vesiculosus (seaweed) extract, Hedera helix (Ivy) extract , Lactamide MEA, Mel ia azadirachta (neem) extract , Mimosa tenuiflora (tepezcohuite) bark extract , Panthenol (vitamin 812), PEG/PPG- 25/25 Dimethicone, Phenoxyethanol , Polyquaternium , Prunus amygdalus dulcis (almond) extract, Rosmarinus officinalis (rosemary) extract , Triethanolamine, Water (aqua) .

Other information

■ Store at 59 to 86 °F (15 to 30 °C).

■ Tamper Evident : DO NOT USE IF SAFETY SEAL ON TUBE IS BROKEN OR MISSING.

Questions

305-505-1116 or www.lovettatc.com